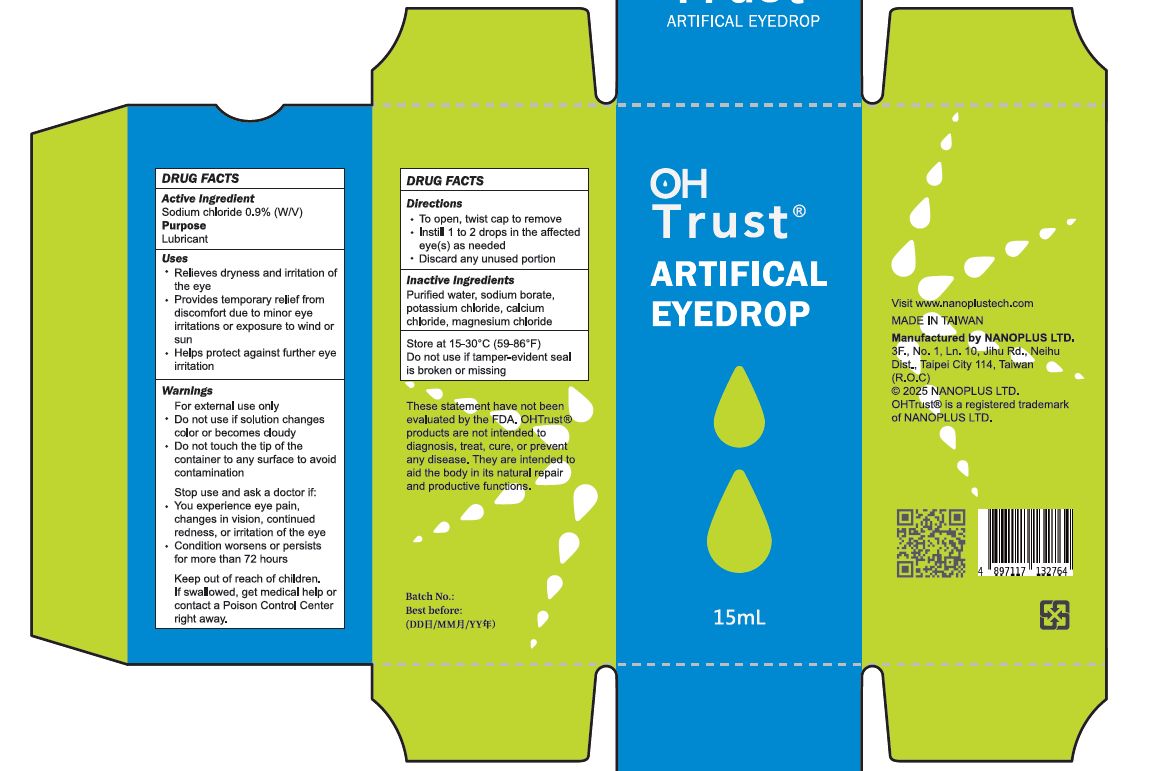 DRUG LABEL: OHTrust Artifical Eyedrop
NDC: 70970-008 | Form: LIQUID
Manufacturer: Nanoplus Limited (Cayman) Taiwan Branch
Category: otc | Type: HUMAN OTC DRUG LABEL
Date: 20250227

ACTIVE INGREDIENTS: SODIUM CHLORIDE 9 mg/1 mL
INACTIVE INGREDIENTS: SODIUM BORATE; CALCIUM CHLORIDE; MAGNESIUM CHLORIDE; POTASSIUM CHLORIDE; WATER

Active Ingredient

Sodium chloride 0.9% (W/V)

Purpose

Lubricant (Artificial Tears)

Warnings

For external use only
- Do not use if solution changes color or becomes cloudy
- Do not touch the tip of the container to any surface to avoid contamination

Uses

- Relieves dryness and irritation of the eye
- Provides temporary relief from discomfort due to minor eye irritations or exposure to wind or sun
- Helps protect against further eye irritation

Stop use and ask a doctor if:

- You experience eye pain, changes in vision, continued redness, or irritation of the eye
- Condition worsens or persists for more than 72 hours

Keep out of reach of children.

If swallowed, get medical help or contact a Poison Control Center right away.

Directions

- To open, twist cap to remove
- Instill 1 to 2 drops in the affected eye(s) as needed
- Discard any unused portion

Other Information

- Store at 15-30°C (59-86°F)
- Do not use if tamper-evident seal is broken or missing

Inactive Ingredients

Purified water, sodium borate, potassium chloride, calcium chloride, magnesium chloride